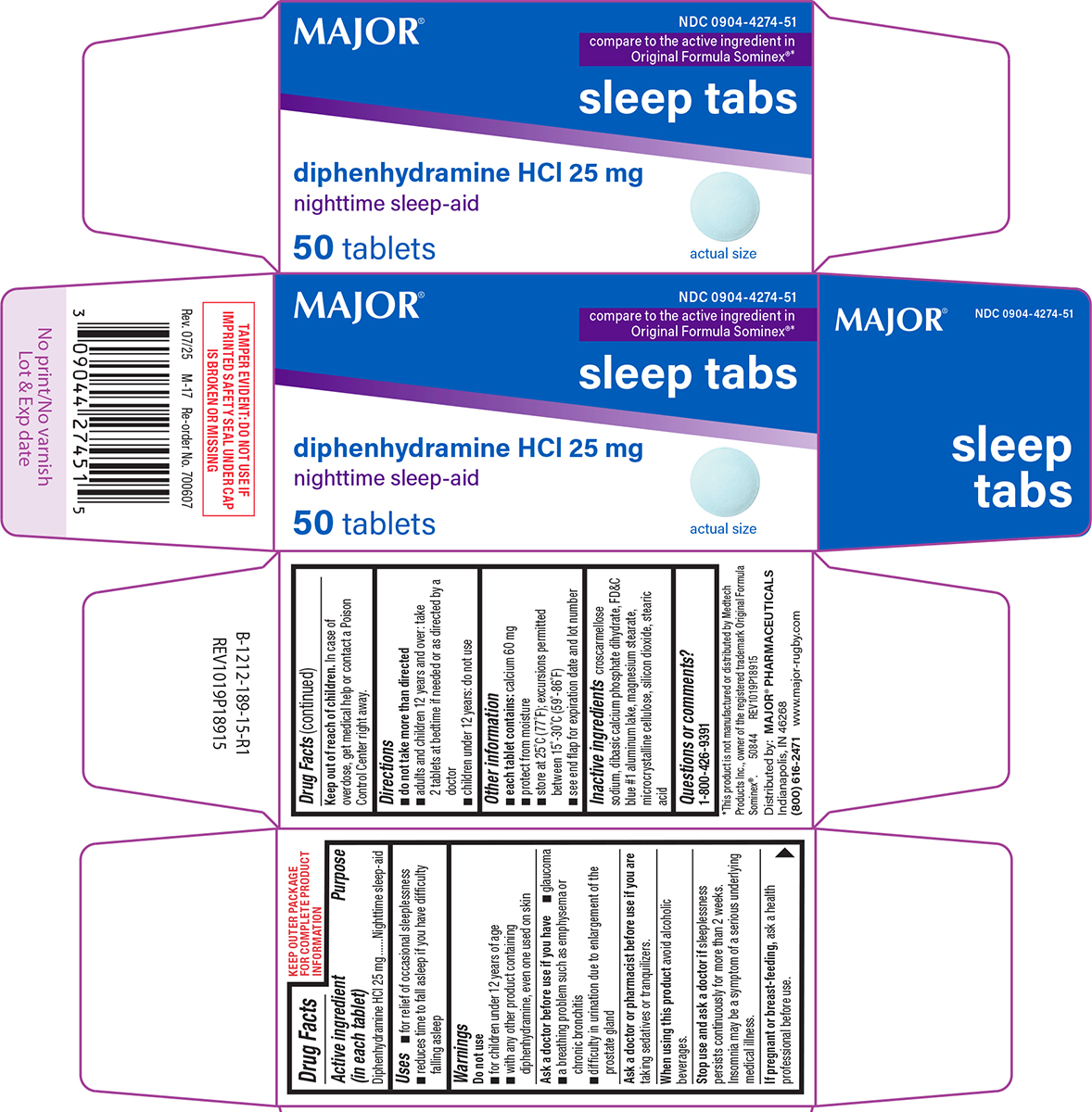 DRUG LABEL: Sleep Tabs
NDC: 0904-4274 | Form: TABLET
Manufacturer: Major Pharmaceuticals
Category: otc | Type: HUMAN OTC DRUG LABEL
Date: 20250812

ACTIVE INGREDIENTS: DIPHENHYDRAMINE HYDROCHLORIDE 25 mg/1 1
INACTIVE INGREDIENTS: CROSCARMELLOSE SODIUM; DIBASIC CALCIUM PHOSPHATE DIHYDRATE; FD&C BLUE NO. 1 ALUMINUM LAKE; MAGNESIUM STEARATE; MICROCRYSTALLINE CELLULOSE; SILICON DIOXIDE; STEARIC ACID

Major 44-189

Active ingredient (in each tablet)

Diphenhydramine HCl 25 mg

Purpose

Nighttime sleep-aid

Uses

- for relief of occasional sleeplessness
- reduces time to fall asleep if you have difficulty falling asleep

Warnings

Do not use

- with any other product containing diphenhydramine, even one used on skin
- for children under 12 years of age

Ask a doctor before use if you have

- a breathing problem such as emphysema or chronic bronchitis
- difficulty in urination due to enlargement of the prostate gland
- glaucoma

Ask a doctor or pharmacist before use if you are

taking sedatives or tranquilizers.

When using this product

avoid alcoholic beverages.

Stop use and ask a doctor if

sleeplessness persists continuously for more than 2 weeks. Insomnia may be a symptom of a serious underlying medical illness.

If pregnant or breast-feeding,

ask a health professional before use.

Keep out of reach of children.

In case of overdose, get medical help or contact a Poison Control Center right away.

Directions

- do not take more than directed
- adults and children 12 years and over: take 2 tablets at bedtime if needed or as directed by a doctor
- children under 12 years: do not use

Other information

- each tablet contains: calcium 60 mg
- protect from moisture
- store at 25ºC (77ºF); excursions permitted between 15º-30ºC (59º-86ºF)
- see end flap for expiration date and lot number

Inactive ingredients

croscarmellose sodium, dibasic calcium phosphate dihydrate, FD&C blue #1 aluminum lake, magnesium stearate, microcrystalline cellulose, silicon dioxide, stearic acid

Questions or comments?

1-800-426-9391

Principal Display Panel

MAJOR®

NDC 0904-4274-51

compare to the active ingredient in
Original Formula Sominex®*

sleep tabs
diphenhydramine HCl 25 mg
nighttime sleep-aid

actual size
50 tablets

TAMPER EVIDENT: DO NOT USE IF
IMPRINTED SAFETY SEAL UNDER CAP
IS BROKEN OR MISSING

*This product is not manufactured or distributed by Medtech
Products Inc., owner of the registered trademark Original Formula
Sominex®. 50844 REV1019P18915
Rev. 07/25 M-17 Re-order No. 700607
Distributed by: MAJOR® PHARMACEUTICALS
Indianapolis, IN 46268
(800) 616-2471 www.major-rugby.com

Rev. 07/25 M-17 Re-order No. 700607

Major 44-189